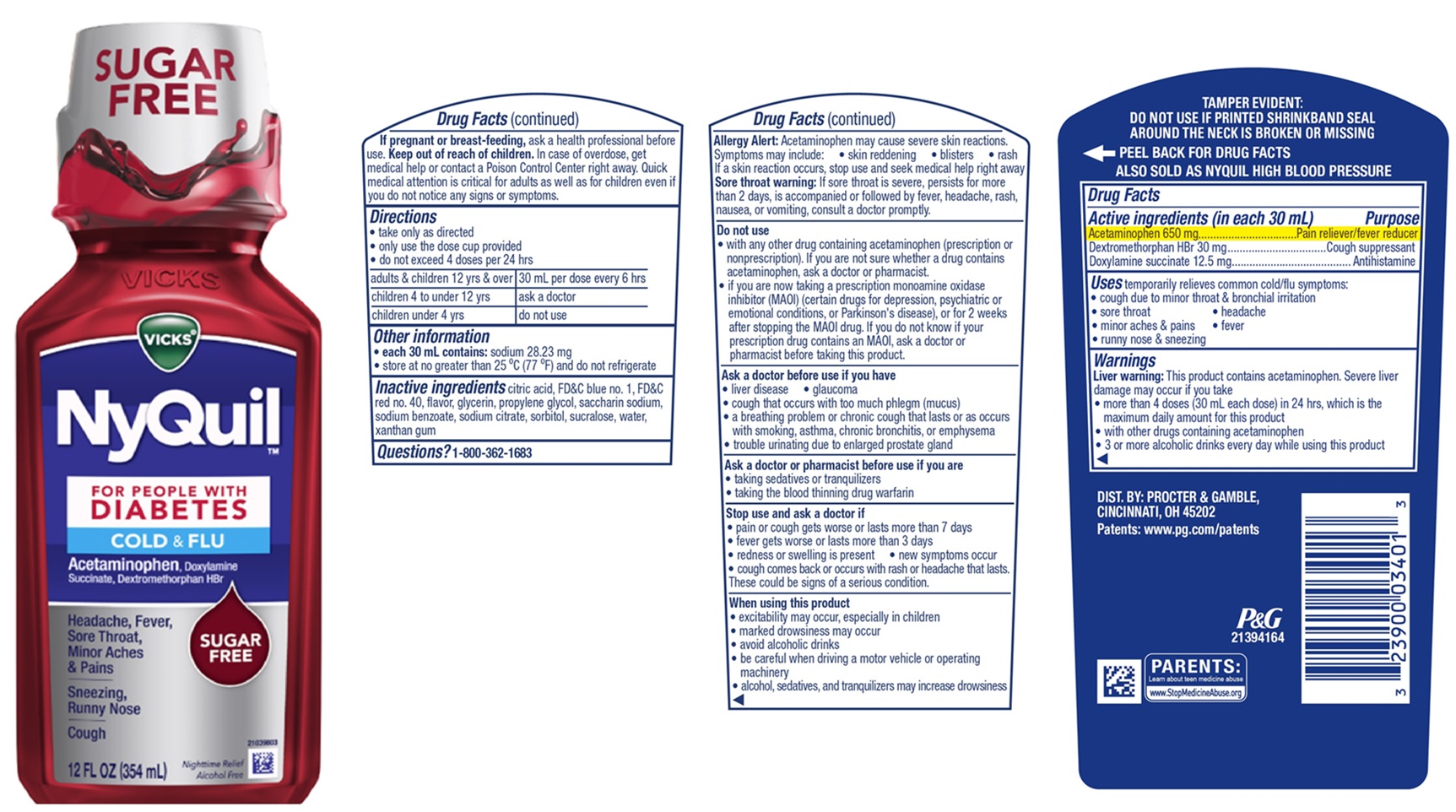 DRUG LABEL: Vicks NyQuil
NDC: 69423-844 | Form: LIQUID
Manufacturer: The Procter & Gamble Manufacturing Company
Category: otc | Type: HUMAN OTC DRUG LABEL
Date: 20251201

ACTIVE INGREDIENTS: ACETAMINOPHEN 650 mg/30 mL; DEXTROMETHORPHAN HYDROBROMIDE 20 mg/30 mL; DOXYLAMINE SUCCINATE 12.5 mg/30 mL
INACTIVE INGREDIENTS: GLYCERIN; PROPYLENE GLYCOL; WATER; SACCHARIN SODIUM; SODIUM CITRATE; FD&C BLUE NO. 1; FD&C RED NO. 40; SODIUM BENZOATE; SORBITOL; XANTHAN GUM; SUCRALOSE

VICKS®NyQuil™
FOR PEOPLE WITH DIABETES COLD & FLU

Drug Facts

Active ingredients (in each 30 mL)

Acetaminophen 650 mg

Dextromethorphan HBr 20 mg

Doxylamine succinate 12.5 mg

Purpose

Pain reliever/fever reducer

Cough suppressant

Antihistamine

Uses

temporarily relieves common cold/flu symptoms:

- cough due to minor throat & bronchial irritation
- sore throat
- headache
- minor aches & pains
- fever
- runny nose & sneezing

Warnings

Liver warning:This product contains acetaminophen. Severe liver damage may occur if you take
• more than 4 doses (30 mL each dose) in 24 hrs, which is the maximum daily amount for this product
• with other drugs containing acetaminophen

• 3 or more alcoholic drinks every day while using this product

Allergy Alert:Acetaminophen may cause severe skin reactions. Symptoms may include:
• skin reddening • blisters • rash

If a skin reaction occurs, stop use and seek medical help right away

Sore throat warning:If sore throat is severe, persists for more than 2 days, is accompanied or followed by fever, headache, rash, nausea, or vomiting, consult a doctor promptly.

Do not use

- with any other drug containing acetaminophen (prescription or nonprescription). If you are not sure whether a drug contains acetaminophen, ask a doctor or pharmacist.

- if you are now taking a prescription monoamine oxidase inhibitor (MAOI) (certain drugs for depression, psychiatric or emotional conditions, or Parkinson's disease), or for 2 weeks after stopping the MAOI drug. If you do not know if your prescription drug contains an MAOI, ask a doctor or pharmacist before taking this product.

Ask a doctor before use if you have

- liver disease
- glaucoma
- cough that occurs with too much phlegm (mucus)
- a breathing problem or chronic cough that lasts or as occurs with smoking, asthma, chronic bronchitis, or emphysema
- trouble urinating due to enlarged prostate gland

Ask a doctor or pharmacist before use if you are

- taking sedatives or tranquilizers
- taking the blood thinning drug warfarin

Stop use and ask a doctor if

- pain or cough gets worse or lasts more than 7 days
- fever gets worse or lasts more than 3 days
- redness or swelling is present
- new symptoms occur
- cough comes back or occurs with rash or headache that lasts.
  These could be signs of a serious condition.

If pregnant or breast-feeding,

ask a health professional before use.

Keep out of reach of children.

OVERDOSAGE

In case of overdose, get medical help or contact a Poison Control Center right away. Quick medical attention is critical for adults as well as for children even if you do not notice any signs or symptoms.

Directions

• take only as directed
• only use dose cup provided
• do not exceed 4 doses per 24 hrs

adults & children 12 yrs & over | 30 mL per dose every 6 hrs
children 4 to under 12 yrs | ask a doctor
children under 4 yrs | do not use

Other information

- each 30 mL dose contains: sodium 28.23 mg
- store at no greater than 25°C (77°F) and do not refrigerate

Inactive ingredients

citric acid, FD&C blue no. 1, FD&C red no. 40, flavor, glycerin, propylene glycol, saccharin sodium, sodium benzoate, sodium citrate, sorbitol, sucralose, water, xanthan gum

Questions?

1-800-362-1683

TAMPER EVIDENT:
DO NOT USE IF PRINTED SHRINKBAND SEAL AROUND THE NECK IS BROKEN OR MISSING.

DIST. BY:

PROCTER & GAMBLE

CINCINNATI, OH 45202

PRINCIPAL DISPLAY PANEL - 354 ml Bottle Label

VICKS®

NyQuil™

FOR PEOPLE WITH DIABETES

COLD & FLU

Acetaminophen,Doxylamine Succinate, Dextromethorphan HBr

Headache, Fever, Sore Throat, Minor Aches & Pains

Sneezing, Runny Nose

Cough

SUGAR FREE

Nighttime Relief

Alcohol Free

12 FL OZ (354 mL)